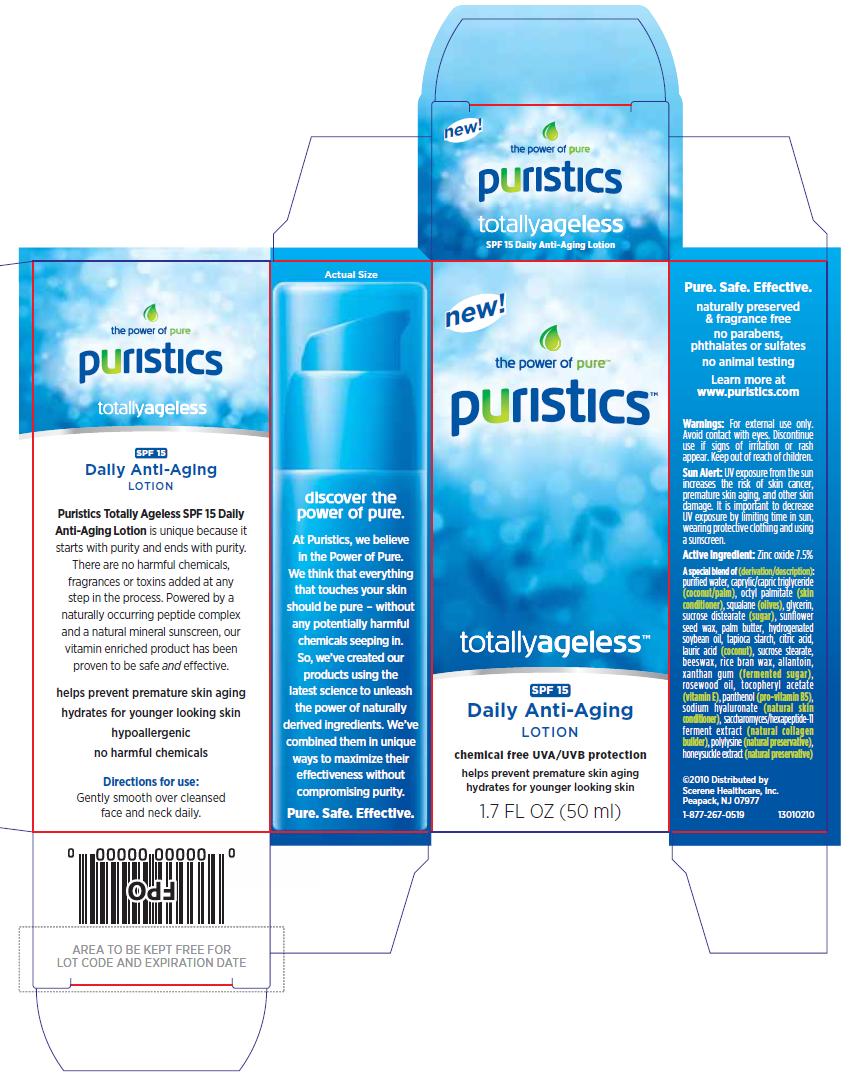 DRUG LABEL: puristics totally ageless spf 15 daily anti-aging 
NDC: 76026-204 | Form: LOTION
Manufacturer: Scerene Healthcare, Inc.
Category: otc | Type: HUMAN OTC DRUG LABEL
Date: 20110207

ACTIVE INGREDIENTS: Zinc Oxide 7.5 mL/100 mL
INACTIVE INGREDIENTS: Water; Medium-chain Triglycerides; Ethylhexyl Palmitate; Squalane; Glycerin; Hydrogenated Soybean Oil; Starch, Tapioca; Citric Acid Monohydrate; Lauric Acid; Sucrose Stearate; Yellow Wax; Allantoin; Xanthan Gum; Rosewood Oil; Panthenol; Hyaluronate Sodium; Lonicera Caprifolium Flower

puristics™ totallyageless™ Daily Anti-Aging Lotion
Drug Facts

Active Ingredient

Zinc oxide 7.5%

Directions

Gently smooth over cleansed face and neck daily.

Warnings

For external use only. Avoid contact with eyes. Discontinue use if signs of irritation or rash appear. Keep out of reach of children.

Principal Panel Display

new!

the power of pure™

puristics™

totallyageless™

SPF 15

Daily Anti-Aging

LOTION

chemical free UVA/UVB protection

helps prevent premature skin aging

hydrates for younger looking skin

1.7 FL OZ (50 ml)

Puristics Totally Ageless SPF 15 Daily Anti-Aging Lotion is unique because it starts with purity and ends with purity. There are no harmful chemicals, fragrances or toxins added at any step in the process. Powered by a naturally occurring peptide complex and a natural mineral sunscreen, our vitamin enriched product has been proven to be safe and effective.

helps prevent premature skin aging

hydrates for younger looking skin

hypoallergenic

no harmful chemicals

Directions for use: Gently smooth over cleansed face and neck daily.

discover the power of pure.

At Puristics, we believe in the Power of Pure. We think that everything that touches your skin should be pure – without any potentially harmful chemicals seeping in. So, we’ve created our products using the latest science to unleash the power of naturally derived ingredients. We’ve combined them in unique ways to maximize their effectiveness without compromising purity.

Pure. Safe. Effective.

naturally preserved & fragrance free

no parabens, phthalates or sulfates

no animal testing

Learn more at www.puristics.com

Warnings: For external use only. Avoid contact with eyes. Discontinue use if signs of irritation or rash appear. Keep out of reach of children.

Sun Alert: UV exposure from the sun increases the risk of skin cancer, premature skin aging, and other skin damage. It is important to decrease UV exposure by limiting time in sun, wearing protective clothing and using a sunscreen.

Active Ingredient: Zinc oxide 7.5%

A special blend of (derivation/description): purified water, caprylic/capric triglyceride (coconut/palm), octyl palmitate (skin conditioner), squalane (olives), glycerin, sucrose distearate (sugar), sunflower seed wax, palm butter, hydrogenated soybean oil, tapioca starch, citric acid, lauric acid (coconut), sucrose stearate, beeswax, rice bran wax, allantoin, xanthan gum (fermented sugar), rosewood oil, tocopheryl acetate (vitamin E), panthenol (pro-vitamin B5), sodium hyaluronate (natural skin conditioner), saccharomyces/hexapeptide-11 ferment extract (natural collagen builder), polylysine (natural preservative), honeysuckle extract (natural preservative)

©2010 Distributed by
Scerene Healthcare, Inc.
Peapack, NJ 07977
1-877-267-0519

13010210